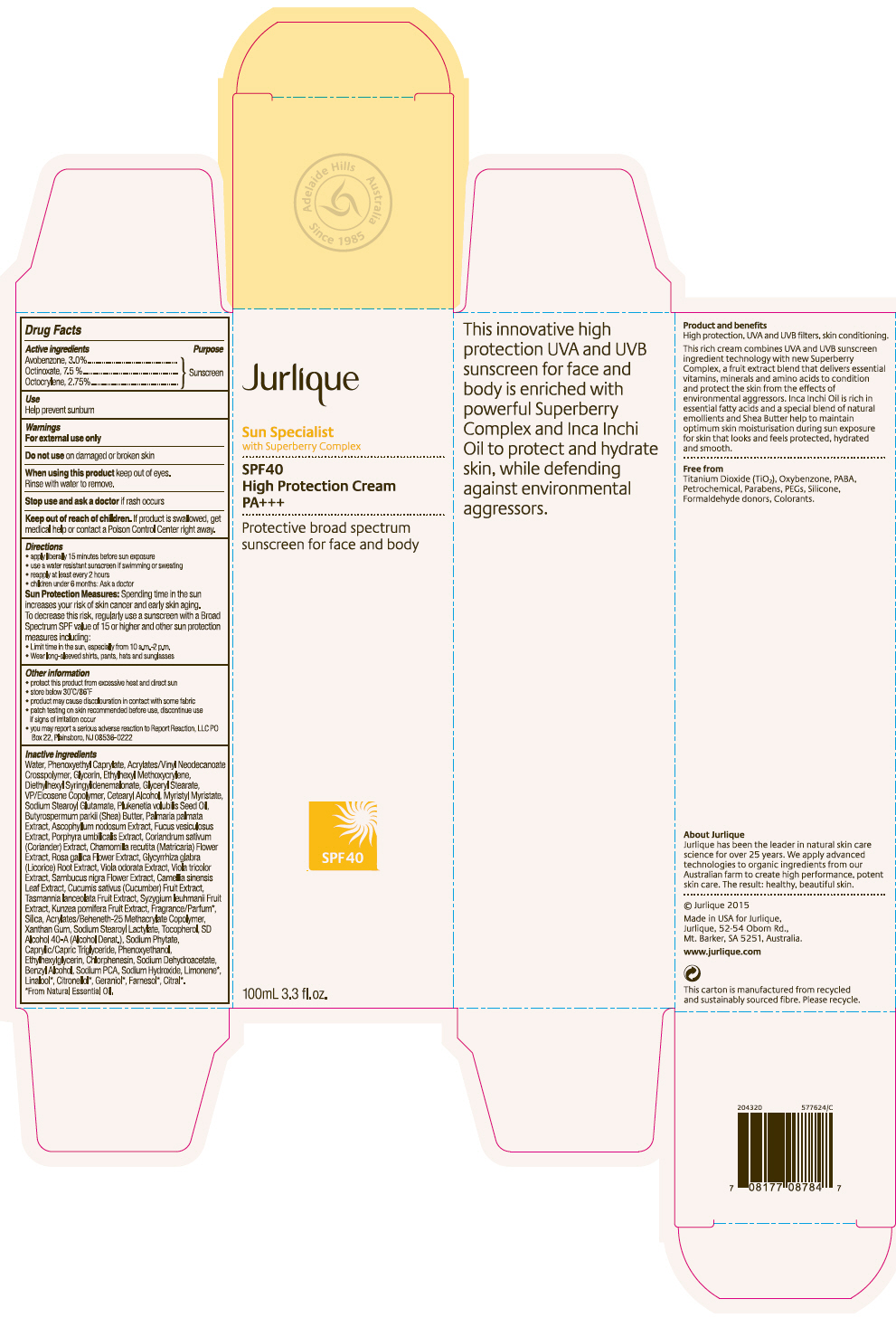 DRUG LABEL: Jurlique SPF40 High Protection Sunscreen
NDC: 68105-006 | Form: CREAM
Manufacturer: Jurlique International
Category: otc | Type: HUMAN OTC DRUG LABEL
Date: 20160725

ACTIVE INGREDIENTS: AVOBENZONE 30 mg/1 mL; OCTINOXATE 75 mg/1 mL; OCTOCRYLENE 27.5 mg/1 mL
INACTIVE INGREDIENTS: Water; Phenoxyethyl Caprylate; ETHYL ACRYLATE/METHACRYLIC ACID/STEARETH-20 METHACRYLATE COPOLYMER; Glycerin; Ethylhexyl Methoxycrylene; Glyceryl Monostearate; Copovidone K25-31; Cetostearyl Alcohol; Myristyl Myristate; Sodium Stearoyl Glutamate; Ascophyllum nodosum; Fucus vesiculosus; Porphyra Umbilicalis; Coriander; Chamomile; Rosa Gallica Flower; Glycyrrhiza Glabra; Viola Odorata; Viola tricolor; European Elderberry; Bancha Tea Leaf/Twig; Cucumber; Silicon Dioxide; Xanthan Gum; Sodium Stearoyl Lactylate; Tocopherol; Alcohol; SODIUM PYRROLIDONE CARBOXYLATE; Medium-Chain Triglycerides; Phenoxyethanol; Ethylhexylglycerin; Sodium Dehydroacetate; Benzyl Alcohol; Phytate Sodium; Sodium Hydroxide

Jurlique SPF40 High Protection Sunscreen

Drug Facts

Active ingredients

Avobenzone, 3.0%
Octinoxate, 7.5 %
Octocrylene, 2.75%

Purpose

Sunscreen

Use

- help prevent sunburn

Warnings

For external use only

Do not use on damaged or broken skin

When using this product keep out of eyes. Rinse with water to remove.

Stop use and ask a doctor if rash occurs

Keep out of reach of children. If product is swallowed, get medical help or contact a Poison Control Center right away.

Directions

- apply liberally 15 minutes before sun exposure
- use a water resistant sunscreen if swimming or sweating
- reapply at least every 2 hours
- children under 6 months: Ask a doctor

Sun Protection Measures. Spending time in the sun increases your risk of skin cancer and early skin aging. To decrease this risk, regularly use a sunscreen with a Broad Spectrum SPF value of 15 or higher and other sun protection measures including:

- Limit time in the sun, especially from 10 a.m.-2 p.m.
- Wear long-sleeved shirts, pants, hats and sunglasses

Other information

- protect this product from excessive heat and direct sun
- Store below 30°C/86°F
- product may cause discolouration in contact with some fabric
- patch testing on skin recommended before use, discontinue use if signs of irritation occur
- you may report a serious adverse reaction to Report Reaction, LLC PO Box 22, Plainsboro, NJ 08536-022

Inactive ingredients

Water, Phenoxyethyl Caprylate, Acrylates/Vinyl Neodecanoate Crosspolymer, Glycerin, Ethylhexyl Methoxycrylene, Diethylhexyl Syringylidenemalonate, Glyceryl Stearate, VP/Eicosene Copolymer, Cetearyl Alcohol, Myristyl Myristate, Sodium Stearoyl Glutamate, Plukenetia volubilis Seed Oil, Butyrospermum parkii (Shea) Butter, Palmaria palmata Extract, Ascophyllum nodosum Extract, Fucus vesiculosus Extract, Porphyra umbilicalis Extract, Corandrum sativum (Coriander) Extract, Chamomilla recutita (Matricaria) Flower Extract, Rosa gallica Flower Extract, Glycyrrhiza glabra (Licorice) Extract, Viola odorata Extract, Viola tricolor Extract, Sambucus nigra Flower Extract, Camellia sinensis Leaf Extract, Cucumis sativus (Cucumber) Fruit Extract, Tasmannia lanceolata Fruit Extract, Syzygium leuhmanii Extract, Kunzea pomifera Fruit Extract, Fragrance/Parfum [From Essential Oil] , Silica, Acrylates/Beheneth-25 methacrylate Copolymer, Xanthan Gum, Sodium Stearoyl Lactylate, Tocopherol, SD Alcohol 40-A (Alcohol Denat.), Sodium Phytate, Caprylic/Capric Triglyceride, Phenoxyethanol, Ethylhexylglycerin, Chlorphenesin, Sodium Dehydroacetate, Benzyl Alcohol, Sodium PCA, Sodium Hydroxide, Limonene, Linalool, Citronellol, Geraniol, Farnesol, Citral.

PRINCIPAL DISPLAY PANEL - 100 mL Tube Carton

Jurlique

Sun Specialist
with Superberry Complex

SPF40
High Protection Cream
PA+++

Protective broad spectrum
sunscreen for face and body

100mL 3.3 fl. oz.